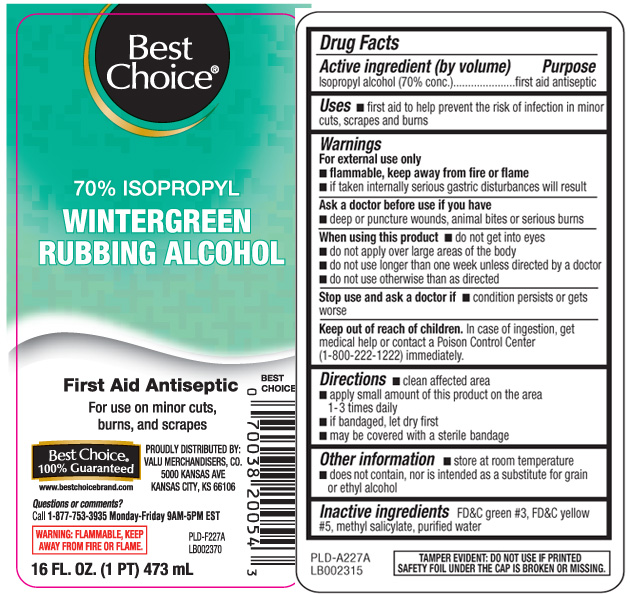 DRUG LABEL: Isopropyl Rubbing Alcohol
NDC: 63941-276 | Form: LIQUID
Manufacturer: Best Choice  (Valu Merchandisers Company)
Category: otc | Type: HUMAN OTC DRUG LABEL
Date: 20250711

ACTIVE INGREDIENTS: ISOPROPYL ALCOHOL 70 mL/100 mL
INACTIVE INGREDIENTS: WATER; FD&C GREEN NO. 3; FD&C YELLOW NO. 5; METHYL SALICYLATE

Drug Facts

Active Ingredients

Isopropyl Alcohol (70% conc.)

Purpose

first aid antiseptic

Uses

- first aid to help prevent the risk of infection in minor cuts, scrapes and burns

Warnings

For external use only

- flammable, keep away from fire or flame
- if taken internally serious gastric disturances will result

Ask a doctor before use if you have

- deep or puncture wounds, animal bites or serious burns

When using this product

- do not get into eyes
- do not apply over large areas of the body
- do not use longer than one week unless directed by a doctor
- do not use otherwise than as directed

Stop use and ask a doctor if

- conditions persists or gets worse

Keep out of reach of children

In case of ingestion, get medical help or contact a Poison Control Center (1-800-222-1222) immediately.

Directions

- clean affected area
- apply small amount of this product on the area 1-3 times daily
- if bandaged, let dry first
- may be covered with a sterile bandage

Other Information

- store at room temperature
- does not contain, nor is intended as a substitute for grain or ehyl alcohol

Inactive Ingredient

FD&C green #3, FD&C yellow #5, methyl salicylate, purified water

Principal Display Panel

70% Isopropyl

Wintergreen Rubbing Alcohol

First Aid Antiseptic

For use on minor cuts, burns, and scrapes

PROUDLY DISTRIBUTED BY:

VALU MERCHANDISERS, CO.

5000 KANSAS AVE

KANSAS CITY, KS 66106

Questions or comments?

Call 1-877-753-3935 Monday-Friday 9AM-5PM EST

www.bestchoicebrand.com

WARNING: FLAMMABLE, KEEP AWAY FROM FIRE OR FLAME

FL OZ (mL)

TAMPER EVIDENT: DO NOT USE IF PRINTED SAFETY FOIL UNDER THE CAP IS BROKEN OR MISSING.

Product Label

Best Choice 70% Isopropyl Wintergreen Rubbing Alcohol